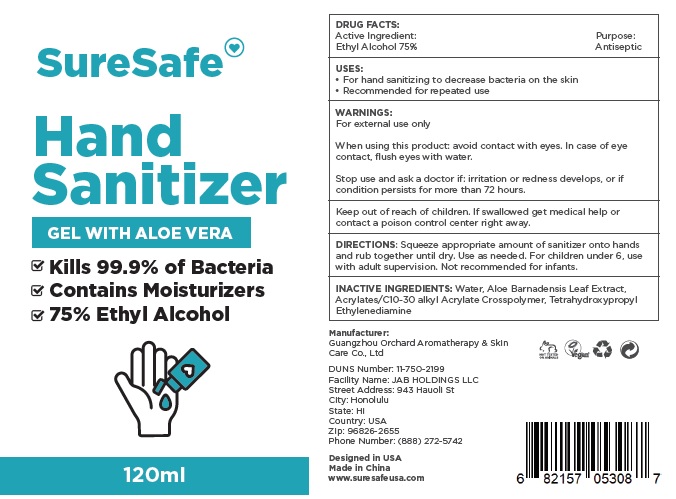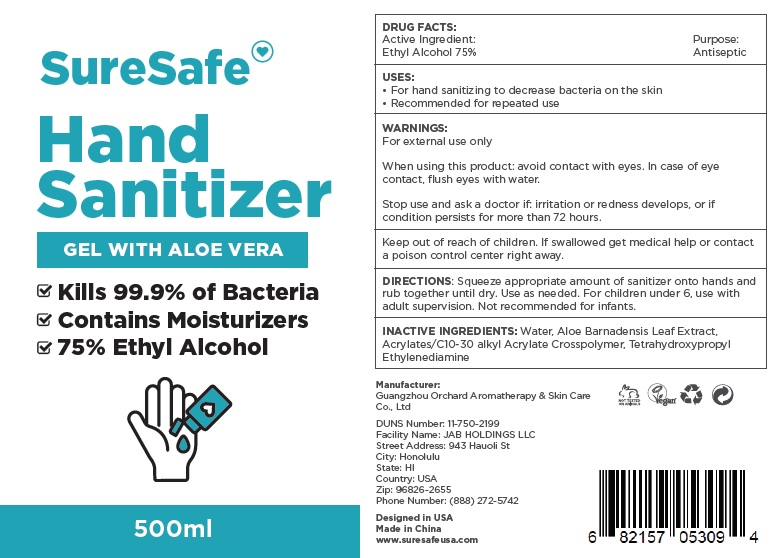 DRUG LABEL: Sure Safe Hand Sanitizer
NDC: 78111-010 | Form: GEL
Manufacturer: Jab Holdings LLC
Category: otc | Type: HUMAN OTC DRUG LABEL
Date: 20200521

ACTIVE INGREDIENTS: ALCOHOL 0.75 mL/1 mL
INACTIVE INGREDIENTS: WATER; ALOE VERA LEAF; CARBOMER INTERPOLYMER TYPE A (ALLYL SUCROSE CROSSLINKED); EDETOL

Sure Safe Hand Sanitizer

Active Ingredient:

Ethyl Alcohol 75%

Purpose:

Antiseptic

USES:

• For hand sanitizing to decrease bacteria on the skin
• Recommended for repeated use

WARNINGS:

For external use only

When using this product:.

avoid contact with eyes. In case of eye contact, flush eyes with water

Stop use and ask a doctor if:

irritation or redness develops, or if condition persists for more than 72 hours.

Keep out of reach of children.

If swallowed get medical help or contact a poison control center right away.

DIRECTIONS:

Squeeze appropriate amount of sanitizer onto hands and rub together until dry. Use as needed. For children under 6, use with adult supervision. Not recommended for infants.

INACTIVE INGREDIENTS:

Water, Aloe Barnadensis Leaf Extract, Acrylates/C10-30 alkyl Acrylate Crosspolymer, Tetrahydroxypropyl Ethylenediamine